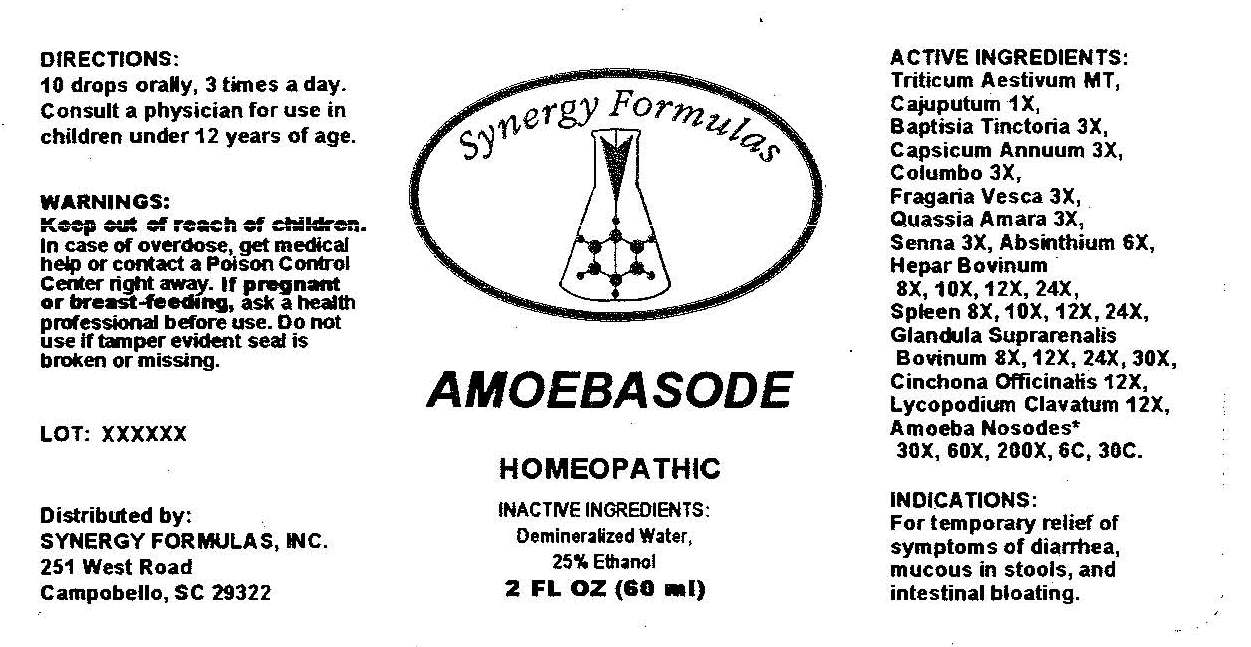 DRUG LABEL: Amoebasode
NDC: 57520-0219 | Form: LIQUID
Manufacturer: Apotheca Company
Category: homeopathic | Type: HUMAN OTC DRUG LABEL
Date: 20110504

ACTIVE INGREDIENTS: WHEAT 1 [hp_X]/1 mL; BAPTISIA TINCTORIA ROOT 3 [hp_X]/1 mL; CAPSICUM 3 [hp_X]/1 mL; JATEORHIZA CALUMBA ROOT 3 [hp_X]/1 mL; FRAGARIA VESCA FRUIT 3 [hp_X]/1 mL; QUASSIA AMARA WOOD 3 [hp_X]/1 mL; SENNA LEAF 3 [hp_X]/1 mL; WORMWOOD 6 [hp_X]/1 mL; CINCHONA OFFICINALIS BARK 12 [hp_X]/1 mL; LYCOPODIUM CLAVATUM SPORE 12 [hp_X]/1 mL; BEEF LIVER 24 [hp_X]/1 mL; BOS TAURUS ADRENAL GLAND 30 [hp_X]/1 mL; CAJUPUT OIL 1 [hp_X]/1 mL; SUS SCROFA SPLEEN 24 [hp_X]/1 mL; AMOEBA PROTEUS 30 [hp_C]/1 mL; GIARDIA LAMBLIA 30 [hp_C]/1 mL
INACTIVE INGREDIENTS: WATER; ALCOHOL

Amoebasode

ACTIVE INGREDIENT

ACTIVE INGREDIENTS: Triticum aestivum 1X, Cajuputum 1X, Baptisia tinctoria 3X, Capsicum annuum 3X, Columbo 3X, Fragaria vesca 3X, Quassia amara 3X, Senna 3X, Absinthium 6X, Hepar bovinum 8X, 10X, 12X, 24X, Spleen 8X, 10X, 12X, 24X, Glandula suprarenalis bovinum 8X, 12X, 24X, 30X, Cinchona officinalis 12X, Lycopodium clavatum 12X, Amoeba 30X, 60X, 200X, 6C, 30C, Giardia 30X, 60X, 200X, 6C, 30C.

PURPOSE

INDICATIONS: For temporary relief of symptoms of diarrhea, mucous in stools, and intestinal bloating.

Keep out of reach of children. In case of overdose, get medical help or contact a Poison Control Center right away.

If pregnant or breast-feeding, ask a health professional before use.

Do not use if tamper evident seal is broken or missing.

DOSAGE AND ADMINISTRATION

DIRECTIONS: 10 drops orally, 3 times a day. Consult a physician for use in children under 12 years of age.

INACTIVE INGREDIENTS: Demineralized Water, 25% Ethanol.

KEEP OUT OF REACH OF CHILDREN. In case of overdose, get medical help or contact a Poison Control Center right away.

INDICATIONS AND USAGE

INDICATIONS: For temporary relief of symptoms of diarrhea, mucous in stools, and intestinal bloating.

QUESTIONS

Distributed by:

SYNERGY FORMULAS, INC.

251 West Road

Campobello, SC 29322

PACKAGE LABEL

Synergy Formulas

AMOEBASODE

HOMEOPATHIC

2 FL OZ (60 ml)